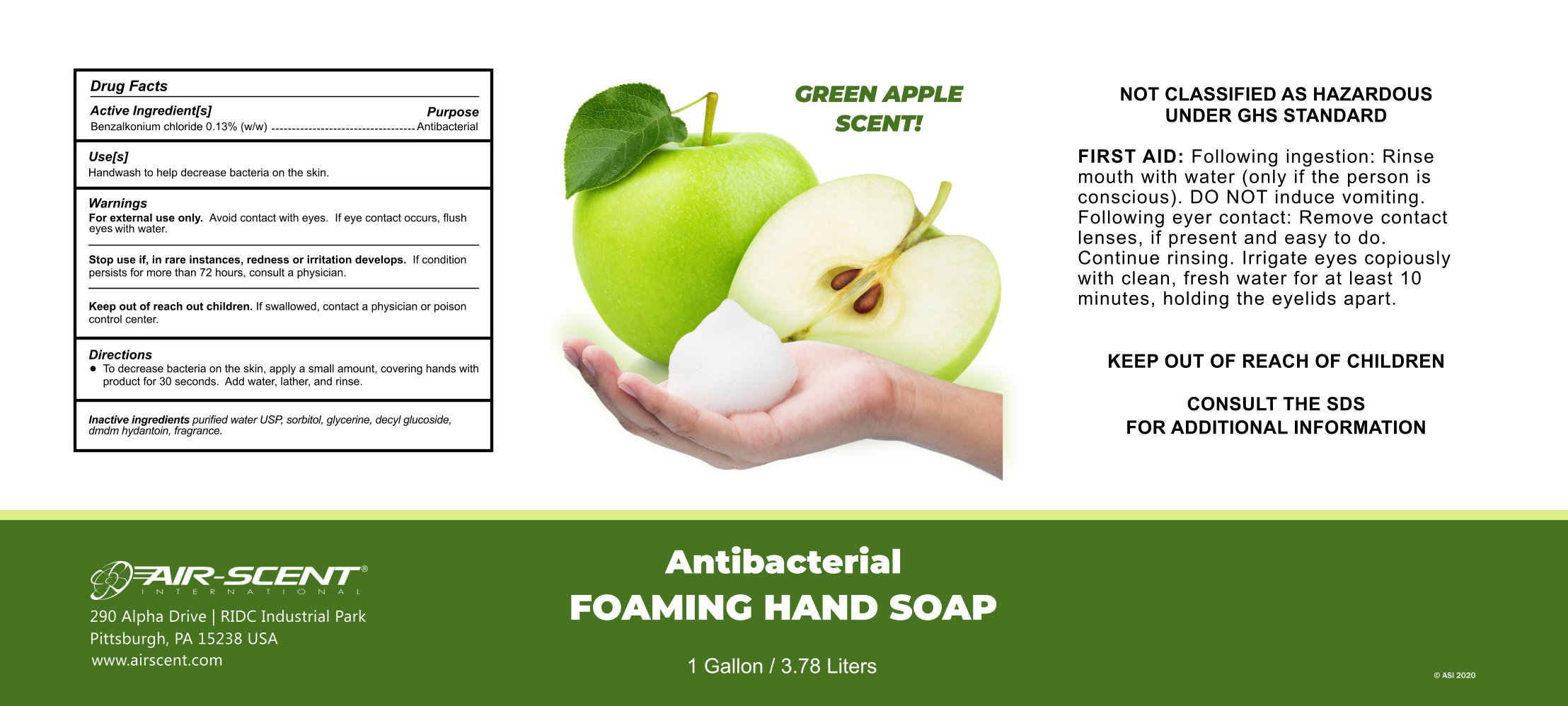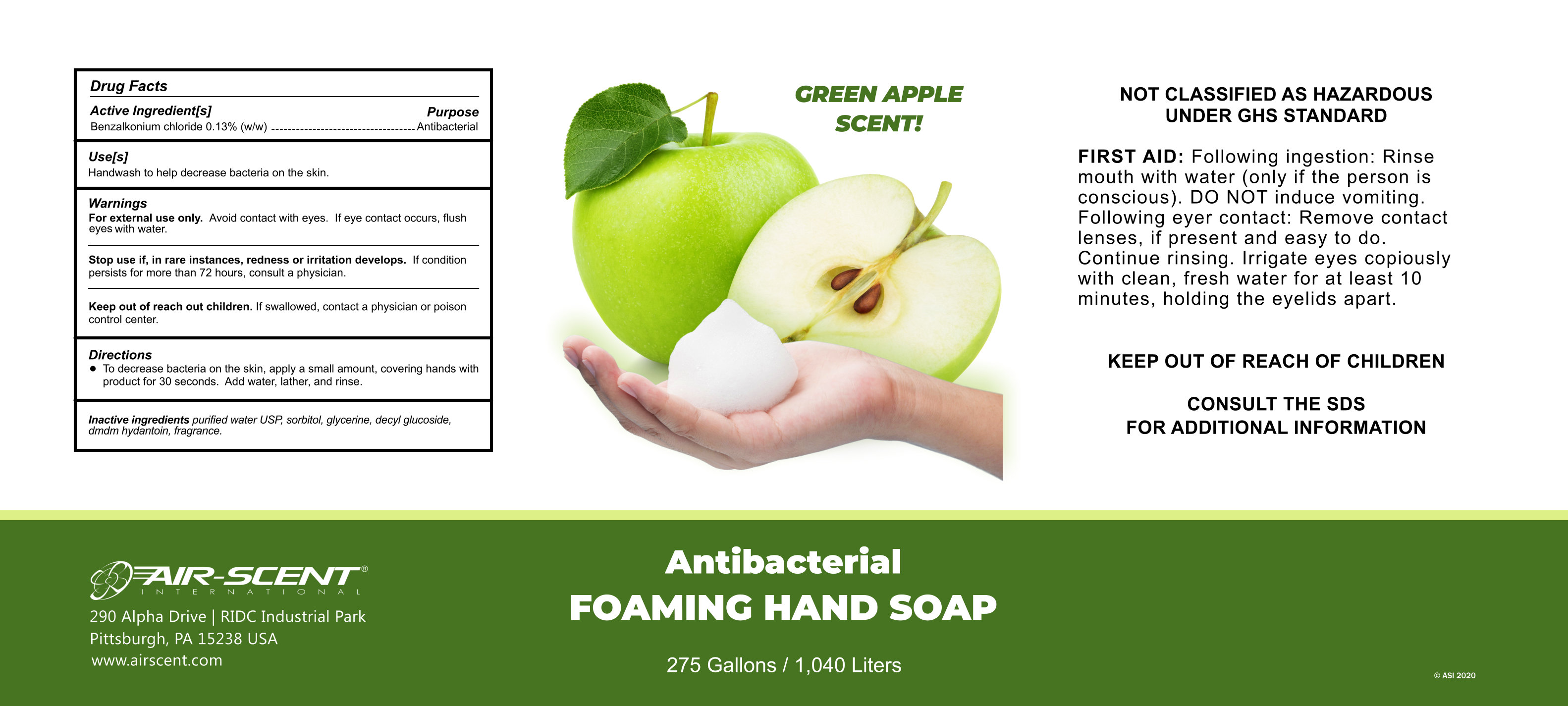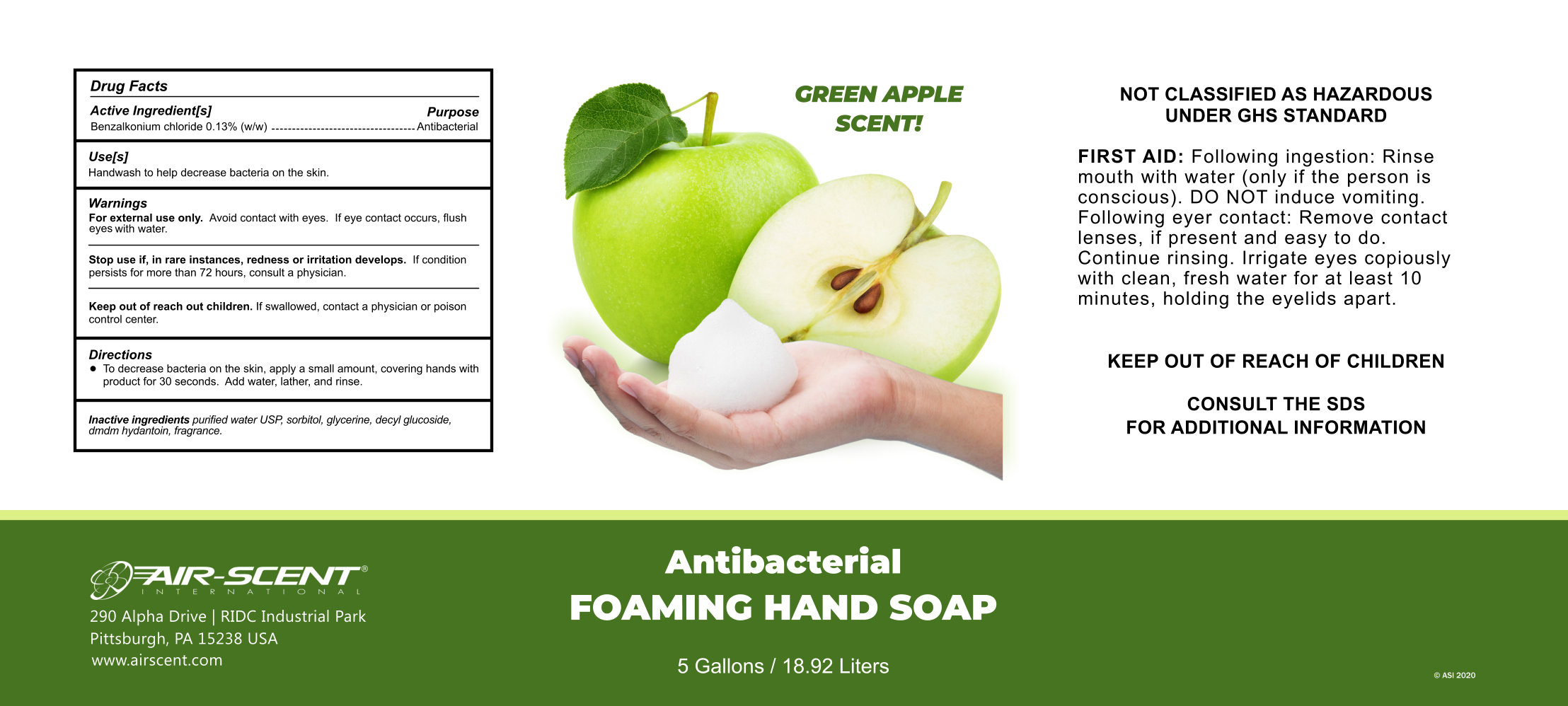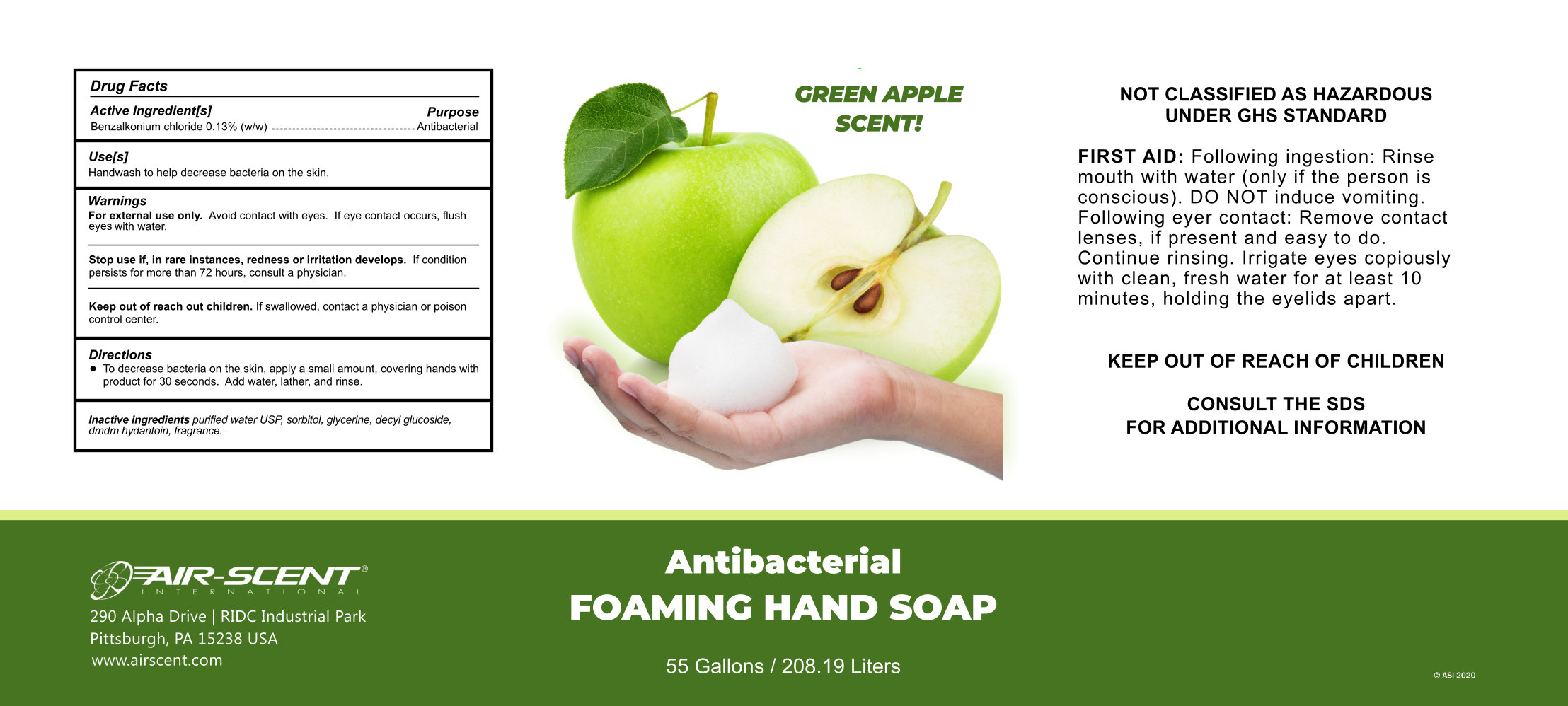 DRUG LABEL: foam 103
NDC: 75009-103 | Form: SOAP
Manufacturer: Alpha Aromatics
Category: otc | Type: HUMAN OTC DRUG LABEL
Date: 20220121

ACTIVE INGREDIENTS: BENZALKONIUM CHLORIDE 0.15 g/100 g
INACTIVE INGREDIENTS: DECYL GLUCOSIDE; GLYCERIN; SORBITOL SOLUTION 70%; DIHYDROMYRCENOL; HEXYL ACETATE; WATER; DMDM HYDANTOIN 1 g/100 g

Antibacterial Green Apple Foaming Hand Soap

Active Ingredient

Benzalkonium Chloride 0.15%(w/w)

Purpose

Anitbacterial

Use

Handwash to help decrease bacteria on the skin

Warnings

For external use only. Avoid contact with eyes. If eye contact occurs, flush eyes with water.

Stop use if, in rare instances, redness or irritation develops. If condition persists for more than 72 hours, consult a physician.

Stop use if, in rare instances, redness or irrtiation develops. If condition persists for more than 72 hours, consult a physician.

Keep out of reach of children. If swallowed, contact a physician or poison control center.

Directions

To decrease bacteria on the skin, apply a small amount, covering hands with product for 30 seconds. Add water, lather, and rinse.

Inactive Ingredients

water, sorbitol, glycerine, decyl glucoside, dmdm hydantoin, fragrance.

Package Label - Principal Display Panel

3.78 L NDC: 75009-103-01

18.92 L NDC: 75009-103-02

208.19 L NDC: 75009-103-03

1040.98 L NDC: 75009-103-04